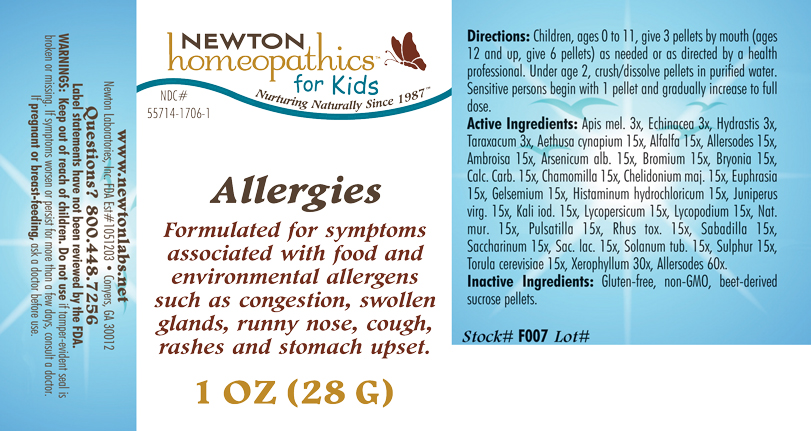 DRUG LABEL: Allergies 
NDC: 55714-1706 | Form: PELLET
Manufacturer: Newton Laboratories, Inc.
Category: homeopathic | Type: HUMAN OTC DRUG LABEL
Date: 20110301

ACTIVE INGREDIENTS: Cow Milk 60 [hp_X]/1 g; Skim Milk 60 [hp_X]/1 g; Cow Milk Fat 60 [hp_X]/1 g; Casein, Lactococcus Lactis Cultured, Aged 60 [hp_X]/1 g; Casein, Lactococcus Lactis Cultured, Penicillium Roqueforti Cultured, Aged 60 [hp_X]/1 g; Casein, Lactococcus Lactis Cultured, Penicillium Camemberti Cultured, Aged 60 [hp_X]/1 g; Egg 60 [hp_X]/1 g; Felis Catus Skin 60 [hp_X]/1 g; Oryctolagus Cuniculus Skin 60 [hp_X]/1 g; Equus Caballus Skin 60 [hp_X]/1 g; Serinus Canaria Feather 60 [hp_X]/1 g; Gallus Gallus Feather 60 [hp_X]/1 g; Anas Platyrhynchos Feather 60 [hp_X]/1 g; Anser Anser Feather 60 [hp_X]/1 g; Melopsittacus Undulatus Feather 60 [hp_X]/1 g; Phasianus Colchicus Feather 60 [hp_X]/1 g; Meleagris Gallopavo Feather 60 [hp_X]/1 g; Felis Catus Hair 60 [hp_X]/1 g; Human Dander 60 [hp_X]/1 g; Canis Lupus Familiaris Hair 60 [hp_X]/1 g; Equus Caballus Hair 60 [hp_X]/1 g; Oryctolagus Cuniculus Hair 60 [hp_X]/1 g; Human Hair 60 [hp_X]/1 g; Human Skin 60 [hp_X]/1 g; Sheep Wool 60 [hp_X]/1 g; Bos Taurus Hair 60 [hp_X]/1 g; Capra Hircus Hair 60 [hp_X]/1 g; Cavia Porcellus Hair 60 [hp_X]/1 g; Mesocricetus Auratus Hair 60 [hp_X]/1 g; Fd&c Yellow No. 5 60 [hp_X]/1 g; D&c Yellow No. 10 60 [hp_X]/1 g; Fd&c Yellow No. 6 60 [hp_X]/1 g; Carmoisine 60 [hp_X]/1 g; Amaranth 60 [hp_X]/1 g; Ponceau 4r 60 [hp_X]/1 g; Fd&c Red No. 3 60 [hp_X]/1 g; Acid Red 1 60 [hp_X]/1 g; Fd&c Blue No. 2 60 [hp_X]/1 g; Sodium Copper Chlorophyllin 60 [hp_X]/1 g; Acid Green 50 60 [hp_X]/1 g; Sodium Benzoate 60 [hp_X]/1 g; Potassium Benzoate 60 [hp_X]/1 g; Propylparaben 60 [hp_X]/1 g; Sodium Dithionate 60 [hp_X]/1 g; 2-phenylphenol 60 [hp_X]/1 g; Sodium Nitrite 60 [hp_X]/1 g; Ascorbic Acid 60 [hp_X]/1 g; Sodium Tripolyphosphate 60 [hp_X]/1 g; Aspartame 60 [hp_X]/1 g; Monosodium Glutamate 60 [hp_X]/1 g; Barley 60 [hp_X]/1 g; Corn 60 [hp_X]/1 g; Wheat Gluten 60 [hp_X]/1 g; Oat 60 [hp_X]/1 g; White Rice 60 [hp_X]/1 g; Rye 60 [hp_X]/1 g; Wheat 60 [hp_X]/1 g; Beef 60 [hp_X]/1 g; Pork 60 [hp_X]/1 g; Lamb 60 [hp_X]/1 g; Chicken 60 [hp_X]/1 g; Turkey 60 [hp_X]/1 g; Quahog, Unspecified 60 [hp_X]/1 g; Crab Leg, Unspecified 60 [hp_X]/1 g; Oyster, Unspecified 60 [hp_X]/1 g; Shrimp, Unspecified 60 [hp_X]/1 g; Scallop, Unspecified 60 [hp_X]/1 g; Xerophyllum Asphodeloides 30 [hp_X]/1 g; Aethusa Cynapium 15 [hp_X]/1 g; Alfalfa 15 [hp_X]/1 g; Aletris Farinosa Root 15 [hp_X]/1 g; Artemisia Vulgaris Root 15 [hp_X]/1 g; Bellis Perennis 15 [hp_X]/1 g; Dysphania Ambrosioides 15 [hp_X]/1 g; Lycopus Virginicus 15 [hp_X]/1 g; Phytolacca Americana Root 15 [hp_X]/1 g; Populus Tremuloides Leaf 15 [hp_X]/1 g; Populus Tremuloides Bark 15 [hp_X]/1 g; Ptelea Trifoliata Bark 15 [hp_X]/1 g; Sambucus Nigra Flowering Top 15 [hp_X]/1 g; Trillium Erectum Root 15 [hp_X]/1 g; Elymus Repens Root 15 [hp_X]/1 g; Urtica Urens 15 [hp_X]/1 g; Wyethia Helenioides Root 15 [hp_X]/1 g; Yucca Filamentosa 15 [hp_X]/1 g; Aconitum Napellus 15 [hp_X]/1 g; Arundo Pliniana Root 15 [hp_X]/1 g; Helianthemum Canadense 15 [hp_X]/1 g; Drosera Rotundifolia 15 [hp_X]/1 g; Solanum Dulcamara Top 15 [hp_X]/1 g; Ledum Palustre Twig 15 [hp_X]/1 g; Onosmodium Virginianum Whole 15 [hp_X]/1 g; Pulsatilla Vulgaris 15 [hp_X]/1 g; Sanguinaria Canadensis Root 15 [hp_X]/1 g; Datura Stramonium 15 [hp_X]/1 g; Atropa Belladonna 15 [hp_X]/1 g; Capsicum 15 [hp_X]/1 g; Hyoscyamus Niger 15 [hp_X]/1 g; Solanum Nigrum Whole 15 [hp_X]/1 g; Tobacco Leaf 15 [hp_X]/1 g; Amanita Muscaria Fruiting Body 15 [hp_X]/1 g; Onion 15 [hp_X]/1 g; Garlic 15 [hp_X]/1 g; Anacardium Occidentale Fruit 15 [hp_X]/1 g; Lycoperdon Utriforme Fruiting Body 15 [hp_X]/1 g; Caffeine 15 [hp_X]/1 g; Cinnamon 15 [hp_X]/1 g; Cynara Scolymus Leaf 15 [hp_X]/1 g; Alpine Strawberry 15 [hp_X]/1 g; Abrus Precatorius Seed 15 [hp_X]/1 g; Glycyrrhiza Glabra 15 [hp_X]/1 g; Mentha Piperita 15 [hp_X]/1 g; Nutmeg 15 [hp_X]/1 g; Lactose 15 [hp_X]/1 g; Black Mustard Seed 15 [hp_X]/1 g; Allylthiourea 15 [hp_X]/1 g; Ustilago Maydis 15 [hp_X]/1 g; Ginger 15 [hp_X]/1 g; Aspergillus Niger Var. Niger 15 [hp_X]/1 g; Cladosporium Herbarum 15 [hp_X]/1 g; Brazil Nut 15 [hp_X]/1 g; Hazelnut, Unspecified 15 [hp_X]/1 g; Peanut 15 [hp_X]/1 g; English Walnut 15 [hp_X]/1 g; Trout, Unspecified 15 [hp_X]/1 g; Cod, Unspecified 15 [hp_X]/1 g; Haddock 15 [hp_X]/1 g; Tuna, Unspecified 15 [hp_X]/1 g; Salmon, Unspecified 15 [hp_X]/1 g; Herring, Unspecified 15 [hp_X]/1 g; Avena Sativa Pollen 15 [hp_X]/1 g; Cynosurus Cristatus Pollen 15 [hp_X]/1 g; Echinochloa Crus-galli Pollen 15 [hp_X]/1 g; Poa Pratensis Pollen 15 [hp_X]/1 g; Anthoxanthum Odoratum Pollen 15 [hp_X]/1 g; Agrostis Gigantea Pollen 15 [hp_X]/1 g; Bromus Secalinus Pollen 15 [hp_X]/1 g; Phleum Pratense Pollen 15 [hp_X]/1 g; Festuca Pratensis Pollen 15 [hp_X]/1 g; Holcus Lanatus Pollen 15 [hp_X]/1 g; Lolium Perenne Pollen 15 [hp_X]/1 g; Fagus Sylvatica Pollen 15 [hp_X]/1 g; Betula Pendula Pollen 15 [hp_X]/1 g; Quercus Alba Pollen 15 [hp_X]/1 g; Fraxinus Excelsior Pollen 15 [hp_X]/1 g; Corylus Americana Pollen 15 [hp_X]/1 g; Populus Nigra Pollen 15 [hp_X]/1 g; Platanus Orientalis Pollen 15 [hp_X]/1 g; Ulmus Glabra Pollen 15 [hp_X]/1 g; Salix Alba Pollen 15 [hp_X]/1 g; Narcissus Pseudonarcissus 15 [hp_X]/1 g; Rosa Canina Flower 15 [hp_X]/1 g; Lilium Candidum Flower 15 [hp_X]/1 g; Dianthus Caryophyllus Flower 15 [hp_X]/1 g; Ulex Europaeus Flower 15 [hp_X]/1 g; Cytisus Scoparius Pollen 15 [hp_X]/1 g; Calluna Vulgaris Pollen 15 [hp_X]/1 g; Crataegus Monogyna Pollen 15 [hp_X]/1 g; House Dust 15 [hp_X]/1 g; Ambrosia Artemisiifolia 15 [hp_X]/1 g; Arsenic Trioxide 15 [hp_X]/1 g; Bromine 15 [hp_X]/1 g; Bryonia Alba Root 15 [hp_X]/1 g; Oyster Shell Calcium Carbonate, Crude 15 [hp_X]/1 g; Matricaria Recutita 15 [hp_X]/1 g; Chelidonium Majus 15 [hp_X]/1 g; Euphrasia Stricta 15 [hp_X]/1 g; Gelsemium Sempervirens Root 15 [hp_X]/1 g; Histamine Dihydrochloride 15 [hp_X]/1 g; Juniperus Virginiana Twig 15 [hp_X]/1 g; Potassium Iodide 15 [hp_X]/1 g; Solanum Lycopersicum 15 [hp_X]/1 g; Lycopodium Clavatum Spore 15 [hp_X]/1 g; Sodium Chloride 15 [hp_X]/1 g; Toxicodendron Pubescens Leaf 15 [hp_X]/1 g; Schoenocaulon Officinale Seed 15 [hp_X]/1 g; Saccharin 15 [hp_X]/1 g; Solanum Tuberosum 15 [hp_X]/1 g; Sulfur 15 [hp_X]/1 g; Saccharomyces Cerevisiae 15 [hp_X]/1 g; Apis Mellifera 3 [hp_X]/1 g; Echinacea, Unspecified 3 [hp_X]/1 g; Goldenseal 3 [hp_X]/1 g; Taraxacum Officinale 3 [hp_X]/1 g; Alopecurus Pratensis Pollen 15 [hp_X]/1 g; Primula Vulgaris 15 [hp_X]/1 g
INACTIVE INGREDIENTS: Sucrose

Allergies

INDICATIONS & USAGE SECTION

Allergies Formulated for symptoms associated with food and environmental allergens such as congestion, swollen glands, runny nose, cough, rashes and stomach upset.

DOSAGE & ADMINISTRATION SECTION

Directions: Children, ages 0 to 11, give 3 pellets by mouth (ages 12 and up, give 6 pellets) as needed or as directed by a health professional. Under age 2, crush/dissolve pellets in purified water. Sensitive persons begin with 1 pellet and gradually increase to full dose.

OTC - ACTIVE INGREDIENT SECTION

Allersodes 60x, Xerophyllum asphodeloides 30x, Aethusa cynapium 15x, Alfalfa 15x, Allersodes 15x, Ambrosia artemisiaefolia 15x, Arsenicum alb. 15x, Bromium 15x, Bryonia 15x, Calc. Carb. 15x, Chamomilla 15x, Chelidonium majus 15x, Euphrasia 15x, Gelsemium 15x, Histaminum hydrochloricum 15x, Juniperus virginiana 15x, Kali iod. 15x, Lycopersicum esculentum 15x, Lycopodium 15x, Nat. mur. 15x, Pulsatilla 15x, Rhus toxicodendron 15x, Sabadilla 15x, Saccharinum 15x, Sac lac. 15x, Solanum tuberosum 15x, Sulphur 15x, Torula cerevisiae 15x, Apis mel. 3x, Echinacea 3x, Hydrastis 3x, Taraxacum 3x.

OTC - PURPOSE SECTION

Formulated for symptoms associated with food and environmental allergens such as congestion, swollen glands, runny nose, cough, rashes and stomach upset.

INACTIVE INGREDIENT SECTION

Inactive Ingredients: Gluten-free, non-GMO, beet-derived sucrose pellets.

QUESTIONS SECTION

www.newtonlabs.net Newton Laboratories, Inc. FDA Est # 1051203 - Conyers, GA 30012
Questions? 1.800.448.7256

WARNINGS SECTION

Warning: Keep out of reach of children. Do not use if tamper-evident seal is broken or missing. If symptoms worsen or persist for more than a few days, consult a doctor. If pregnant or breast-feeding, ask a doctor before use.

OTC - PREGNANCY OR BREAST FEEDING SECTION

If pregnant or breast-feeding, ask a doctor before use.

OTC - KEEP OUT OF REACH OF CHILDREN SECTION

Keep out of reach of children.